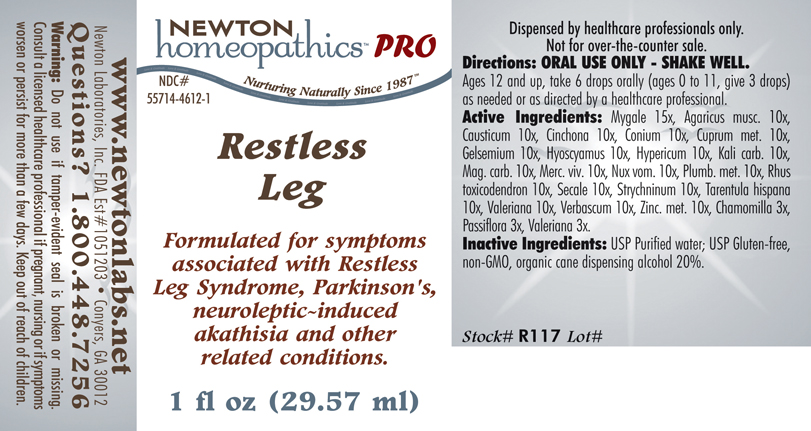 DRUG LABEL: Restless Leg 
NDC: 55714-4612 | Form: LIQUID
Manufacturer: Newton Laboratories, Inc.
Category: homeopathic | Type: HUMAN PRESCRIPTION DRUG LABEL
Date: 20110601

ACTIVE INGREDIENTS: Avicularia Avicularia 15 [hp_X]/1 mL; Amanita Muscaria Var. Muscaria Fruiting Body 10 [hp_X]/1 mL; Causticum 10 [hp_X]/1 mL; Cinchona Officinalis Bark 10 [hp_X]/1 mL; Conium Maculatum Flowering Top 10 [hp_X]/1 mL; Copper 10 [hp_X]/1 mL; Gelsemium Sempervirens Root 10 [hp_X]/1 mL; Hyoscyamus Niger 10 [hp_X]/1 mL; Hypericum Perforatum 10 [hp_X]/1 mL; Potassium Carbonate 10 [hp_X]/1 mL; Magnesium Carbonate 10 [hp_X]/1 mL; Mercury 10 [hp_X]/1 mL; Strychnos Nux-vomica Seed 10 [hp_X]/1 mL; Lead 10 [hp_X]/1 mL; Toxicodendron Pubescens Leaf 10 [hp_X]/1 mL; Claviceps Purpurea Sclerotium 10 [hp_X]/1 mL; Strychnine 10 [hp_X]/1 mL; Lycosa Tarantula 10 [hp_X]/1 mL; Valerian 10 [hp_X]/1 mL; Verbascum Thapsus 10 [hp_X]/1 mL; Zinc 10 [hp_X]/1 mL; Matricaria Recutita 3 [hp_X]/1 mL; Passiflora Incarnata Flowering Top 3 [hp_X]/1 mL
INACTIVE INGREDIENTS: Alcohol

Restless Leg

INDICATIONS & USAGE SECTION

Restless Leg Formulated for symptoms associated with Restless Leg Syndrome, Parkinson's, neuroleptic~induced akathisia and other related conditions.

DOSAGE & ADMINISTRATION SECTION

Directions: ORAL USE ONLY - SHAKE WELL. Ages 12 and up, take 6 drops orally (ages 0 to 11, give 3 drops) as needed or as directed by a healthcare professional.

ACTIVE INGREDIENT SECTION

Mygale 15x, Agaricus musc. 10x, Causticum 10x, Cinchona 10x, Conium 10x, Cuprum met. 10x, Gelsemium 10x, Hyoscyamus 10x, Hypericum 10x, Kali carb. 10x ,Mag. carb. 10x, Merc. viv. 10x, Nux vom. 10x, Plumb. met. 10x, Rhus toxicodendron 10x, Secale 10x, Strychninum 10x, Tarentula hispana 10x, Valeriana 10x, Verbascum 10x, Zinc. met. 10x, Chamomilla 3x, Passiflora 3x, Valeriana 3x.

PURPOSE SECTION

Formulated for symptoms associated with Restless Leg Syndrome, Parkinson's, neuroleptic-induced akathisia and other related conditions.

INACTIVE INGREDIENT SECTION

Inactive Ingredients: USP Purified water; USP Gluten-free,non-GMO, organic cane dispensing alcohol 20%.

QUESTIONS? SECTION

www.newtonlabs.net Newton Laboratories, Inc. FDA Est # 1051203 - Conyers, GA 30012
Questions? 1.800.448.7256

WARNINGS SECTION

Warning: Do not use if tamper - evident seal is broken or missing. Consult a licensed healthcare professional if pregnant, nursing or if symptoms worsen or persist for more than a few days. Keep out of reach of children.

PREGNANCY OR BREAST FEEDING SECTION

Consult a licensed healthcare professional if pregnant, nursing or if symptoms worsen or persist for more than a few days.

KEEP OUT OF REACH OF CHILDREN SECTION

Keep out of reach of children